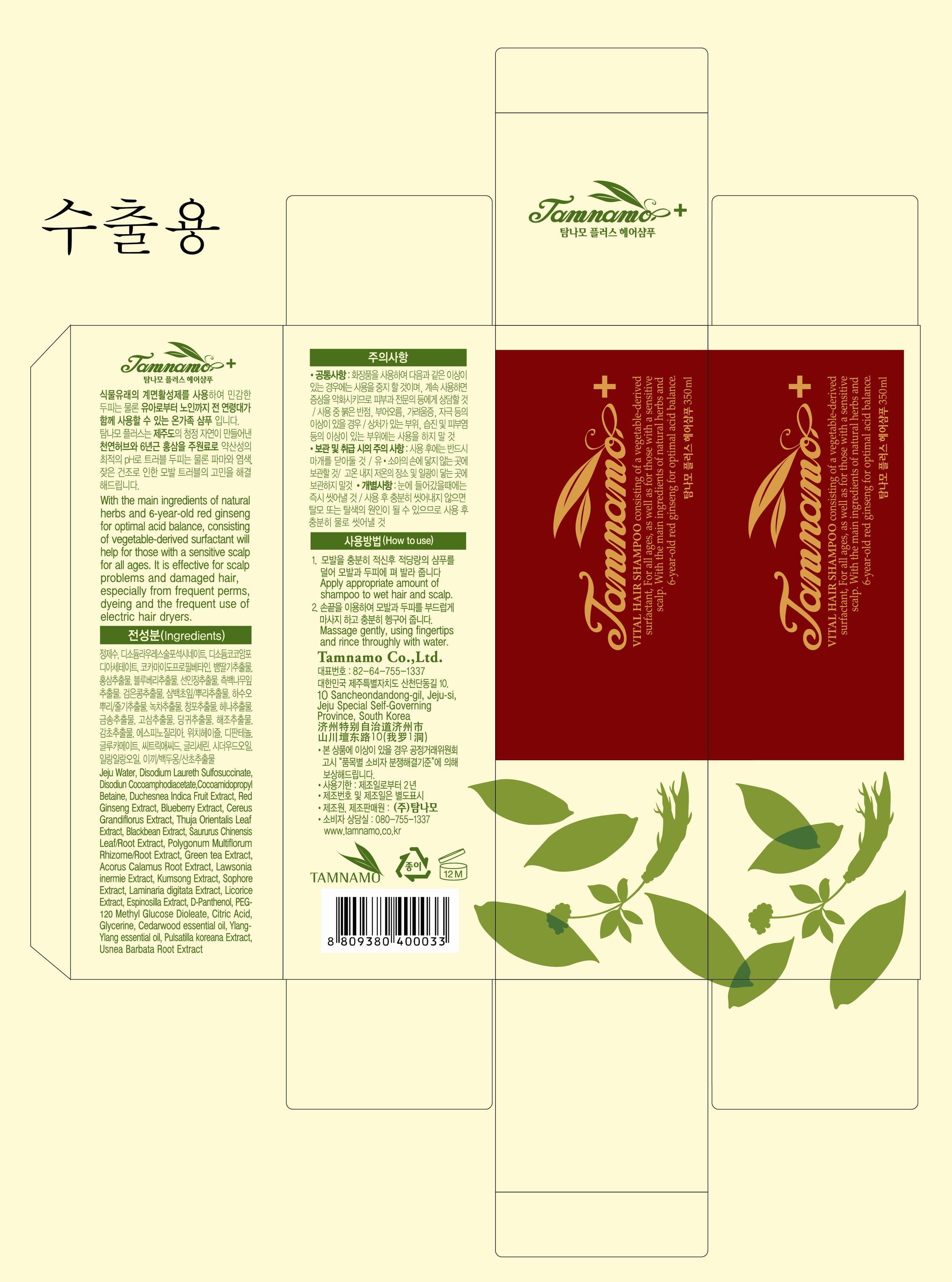 DRUG LABEL: TAMNAMO PLUS VITAL HAIR
NDC: 60344-2001 | Form: SHAMPOO
Manufacturer: Tamnamo Co., Ltd
Category: otc | Type: HUMAN OTC DRUG LABEL
Date: 20130826

ACTIVE INGREDIENTS: GLYCERIN 0.01 g/1 mL
INACTIVE INGREDIENTS: WATER; DISODIUM LAURETH SULFOSUCCINATE; LICORICE; CITRIC ACID MONOHYDRATE

Drug Facts

ACTIVE INGREDIENT

glycerin

INACTIVE INGREDIENT

Water, Disodium Laureth Sulfosuccinate, Sodium Cocoamphoacetate, Cocoamidopropyl Betaine, Duchesnea Indica Fruit Extract, Red Ginseng Extract, Blueberry Extract, Cereus Grandiflorus Extract, Thuja Orientalis Leaf Extract, Blackbean Extract, Saururus Chinensis Leaf/Root Extract, Polygonum Multiflorum Rhizome/Root Extract, Green tea Extract, Acorus Calamus Root Extract, Lawsonia inermie Extract, Kumsong Extract, Sophore Extract, Laminaria digitata Extract, Licorice Extract, Espinosilla Extract, D-Panthenol, PEG-120 Methyl Glucose Dioleate, Citric Acid, Glycerine, Cedarwood essential oil, Ylang-Ylang essential oil, Pulsatilla koreana Extract, Usnea Barbata Root Extract

PURPOSE

supplying nutrients and moisture to scalp and hair

keep out of reach of the children

INDICATIONS AND USAGE

apply appropriate amount of shampoo to wet hair and scalp
massage gently, using fingertips and rinse throughly with water

WARNINGS

- Stop using if sensitivities occurs and consult with dermatologist
- sensitivities such as red marks, intumescence, urtication, irritation during use
- Do not store at high and low temperatures and avoid sunlight.

DOSAGE AND ADMINISTRATION

for external use only